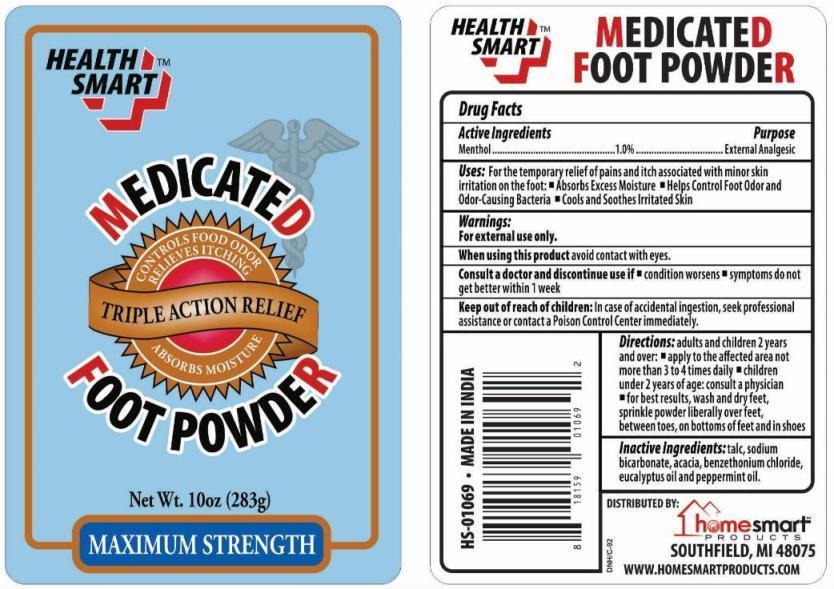 DRUG LABEL: Health Smart Medicated Foot
NDC: 52862-021 | Form: POWDER
Manufacturer: International Wholesale Inc dba Home Smart Products
Category: otc | Type: HUMAN OTC DRUG LABEL
Date: 20241219

ACTIVE INGREDIENTS: MENTHOL 1 g/100 g
INACTIVE INGREDIENTS: TALC; SODIUM BICARBONATE; ACACIA; BENZETHONIUM CHLORIDE; EUCALYPTUS OIL; PEPPERMINT OIL

Health Smart Medicated Foot Powder

Active Ingredient

Menthol 1.0%

Purpose

External Analgesic

Uses

For the temporary relief of pains and itch associated with minor skin irritation on the foot:

- Absorbs Excess Moisture
- Helps Control Foot Odor and Odor-Causing Bacteria
- Cools and Soothes Irritated Skin

Warnings

For external use only.

When using this productavoid contact with eyes.

Consult a doctor and discontinue use if

- condition worsens
- symptoms do not get better within 1 week.

Keep out of reach of children

In case of accidental ingestion, seek professional assistance or contact a Poison Control Center immediately.

Directions

- adults and children 2 years and over: apply to the affected area not more than 3 or 4 times daily.
- children under 2 years of age: consult a physician.
- for best results, wash and dry feet, sprinkle powder liberally over feet, between toes, on bottoms of feet and in shoes.

Inactive Ingredients

talc, sodium bicarbonate, acacia, benzethonium chloride, eucalyptus oil and peppermint oil.

PRINCIPAL DISPLAY PANEL

HEALTH SMART MEDICATED FOOT POWDER

NET WT. 10 OZ. (283g)